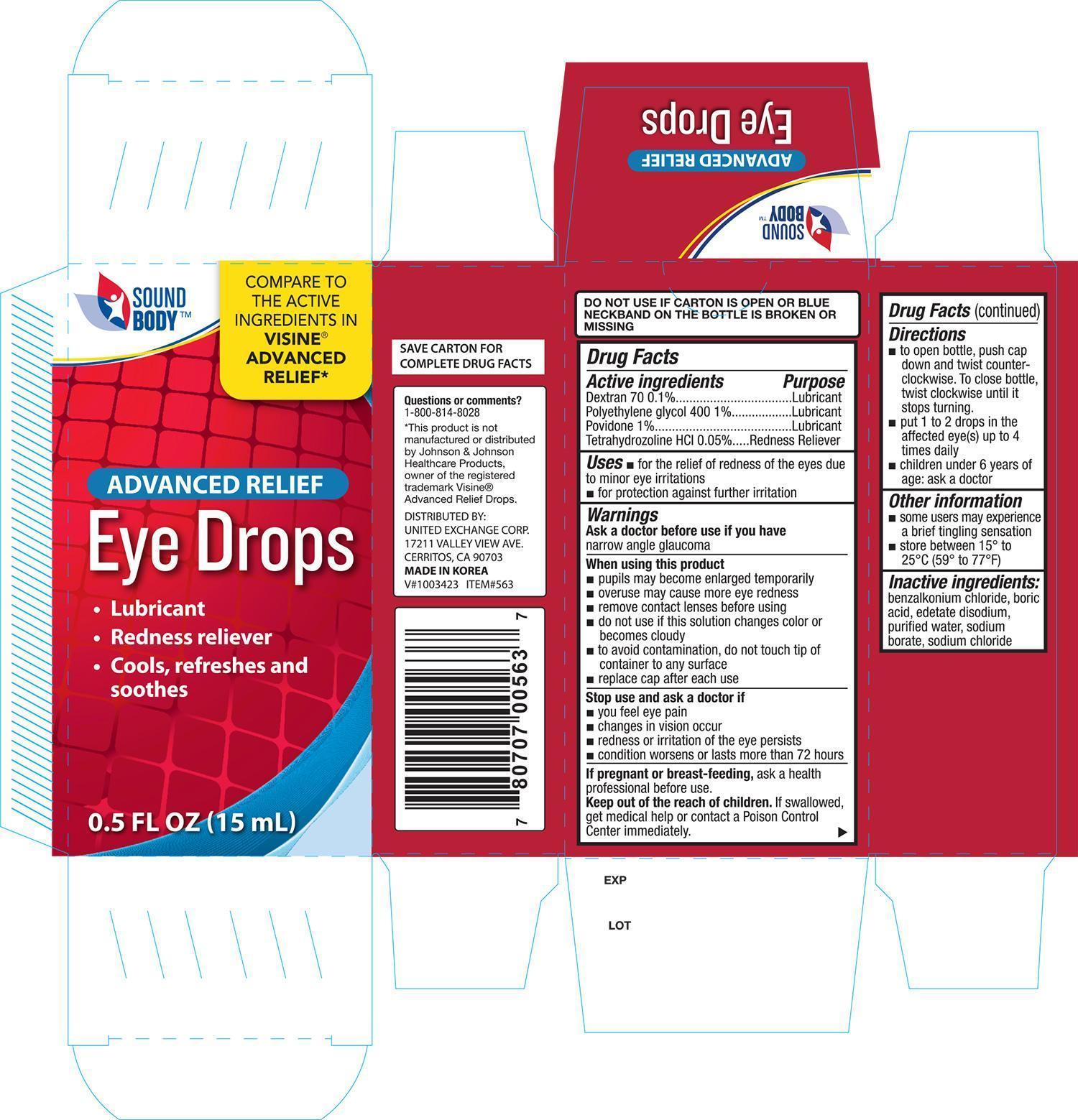 DRUG LABEL: SoundBody Advanced Relief
NDC: 65923-637 | Form: SOLUTION/ DROPS
Manufacturer: United Exchange Corp.
Category: otc | Type: HUMAN OTC DRUG LABEL
Date: 20141125

ACTIVE INGREDIENTS: DEXTRAN 70 1 mg/1 mL; POLYETHYLENE GLYCOL 400 10 mg/1 mL; POVIDONE 10 mg/1 mL; TETRAHYDROZOLINE HYDROCHLORIDE .5 mg/1 mL
INACTIVE INGREDIENTS: BENZALKONIUM CHLORIDE; BORIC ACID; EDETATE DISODIUM; WATER; SODIUM BORATE; SODIUM CHLORIDE

Active ingredients Purpose

Dextran 70 0.1%.............................................. Lubricant

Polyethylene glycol 400 1%................................ Lubricant

Povidone 1%.................................................... Lubricant

Tetrahydrozoline HCI 0.05%............................... Redness reliever

Uses

- for the relief of redness of the eyes due to minor eye irritations
- for protection against further irritation

Ask a doctor before use if you have narrow angle glaucoma

When using this product

- pupils may become enlarged temporarily
- overuse may cause more eye redness
- remove contact lenses before using
- do not use if this solution changes color or becomes cloudy
- to avoid contamination, do not touch tip of container to any surface
- replace cap after each use

Stop use and ask a doctor if

- you feel eye pain
- changes in vision occur
- redness or irritation of the eye lasts
- condition worsens or lasts more than 72 hours

PREGNANCY OR BREAST FEEDING

If pregnant or breast feeding, ask a health professional before use

Keep out of reach of children. If swallowed, get medical help or contact a Poision Control Center right away

Directions

- to open bottle, push cap down and twist counterclockwise. To close bottle, twist clockwise until it stops turning.
- put 1 to 2 drops in the affected eye(s) up to 4 times daily
- children under 6 years of age: ask a doctor

Other information

- some users may experience a brief tingling sensation
- store at 15°-25°C (59°-77°F)

Inactive ingredients

benzalkonium chloride, boric acid, edetate disodium, purified water, sodium borate, sodium chloride

DOSAGE AND ADMINISTRATION

DISTRIBUTED BY:

UNITED EXCHANGE CORP.

17211 VALLEY VIEW AVE.

CERRITOS, CA 90703 USA

Made in Korea